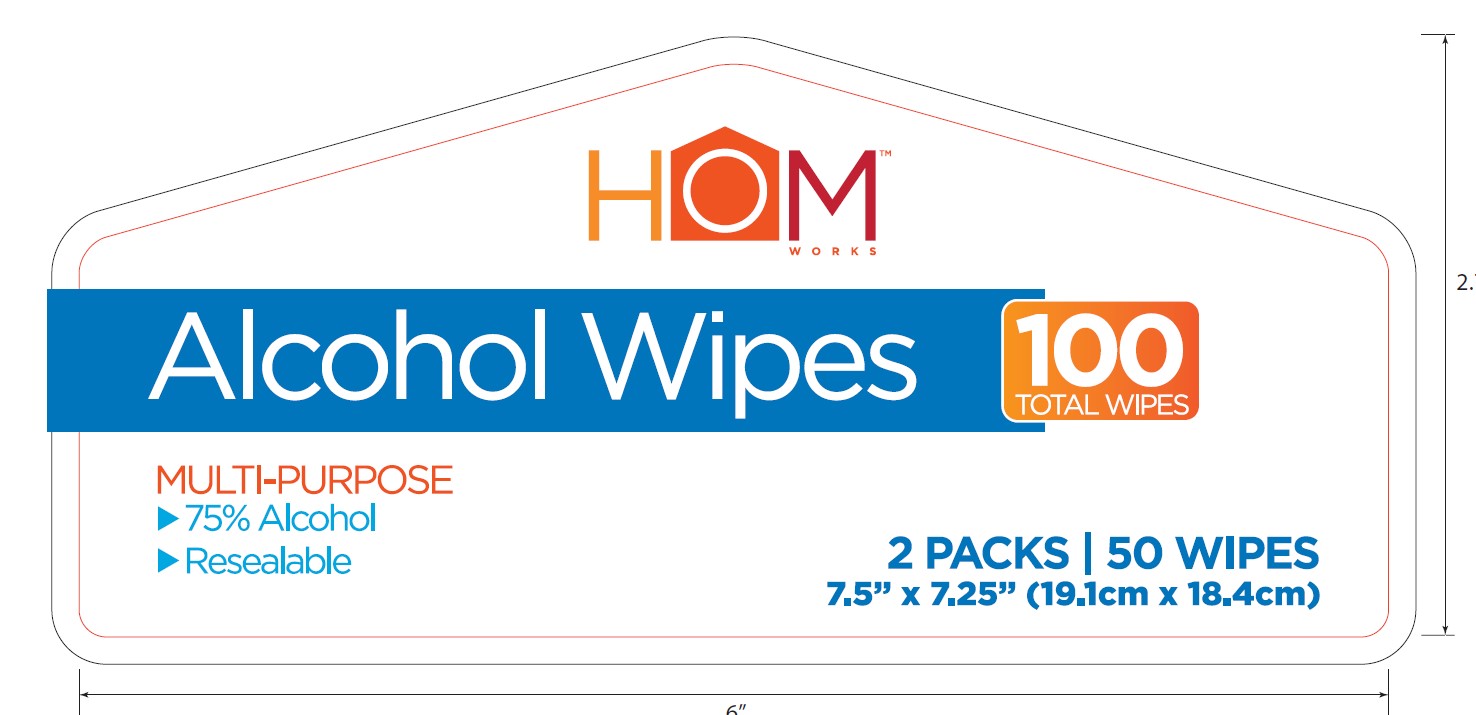 DRUG LABEL: Homworks Alcohol Wipes Multipurpose
NDC: 82131-252 | Form: SWAB
Manufacturer: Acadian Crossing Consumer Products, LLC.
Category: otc | Type: HUMAN OTC DRUG LABEL
Date: 20260126

ACTIVE INGREDIENTS: ALCOHOL 75 mL/75 mL
INACTIVE INGREDIENTS: WATER; GLYCERIN

DOSAGE AND ADMINISTRATION

Directions: Single use wipes for hands. Close properly after dispensing to maintain purity, as alcohol by its nature evaporates quickly. Dispose of properly. DO NOT FLUSH. Apply thoroughly to hands to cover all surfaces. Rub hands together until dry.

WARNINGS

Warnings: For external use only: hands, general cleansing. Does not replace wipes used for medical procedures. Flammable; keep away from fire or flame. Do not ingest.

Inactive Ingredients: Glycerol, Water.

INDICATIONS AND USAGE

Uses: To help reduce bacteria that potentially can cause disease.

Keep out of reach of children: If swallowed, get medical help or contact a poison control center right away.

PURPOSE

Antiseptic

Active Ingredient

Ethyl Alcohol 75% v/v